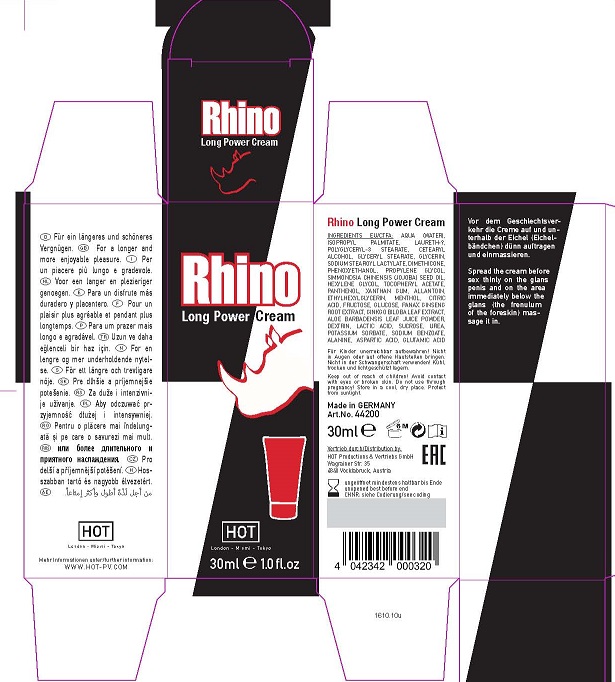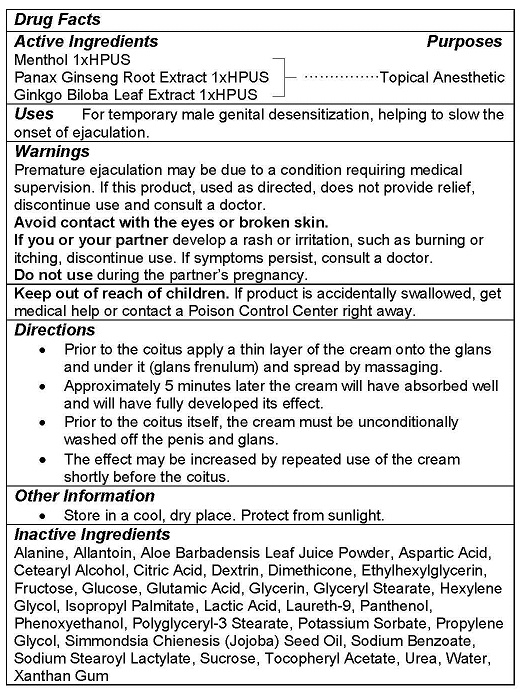 DRUG LABEL: RHINO LONG POWER
NDC: 71326-101 | Form: CREAM
Manufacturer: HOT PRODUCTIONS AND VERTRIEBS GMBH
Category: homeopathic | Type: HUMAN OTC DRUG LABEL
Date: 20231005

ACTIVE INGREDIENTS: MENTHOL 1 g/100 mL; ASIAN GINSENG 1 g/100 mL; GINKGO 1 g/100 mL
INACTIVE INGREDIENTS: ALLANTOIN; ALOE VERA LEAF; ALANINE; ASPARTIC ACID; CETOSTEARYL ALCOHOL; ANHYDROUS CITRIC ACID; ICODEXTRIN; DIMETHICONE; ETHYLHEXYLGLYCERIN; FRUCTOSE; DEXTROSE, UNSPECIFIED FORM; GLUTAMIC ACID; GLYCERIN; GLYCERYL MONOSTEARATE; HEXYLENE GLYCOL; ISOPROPYL PALMITATE; LACTIC ACID; POLIDOCANOL; PANTHENOL; PHENOXYETHANOL; POLYGLYCERYL-3 DISTEARATE; POTASSIUM SORBATE; PROPYLENE GLYCOL; JOJOBA OIL; SODIUM BENZOATE; SODIUM STEAROYL LACTYLATE; SUCROSE; .ALPHA.-TOCOPHEROL ACETATE; UREA; WATER; XANTHAN GUM

HOT PRODUCTS - Rhino Long Power Cream (71326-101)

ACTIVE INGREDIENTS

Menthol 1xHPUS
Panax Ginseng Root Extract 1xHPUS
Ginkgo Biloba Leaf Extract 1xHPUS

PURPOSE

Topical Anesthetic

USE

For temporary male genital desensitization, helping to slow the onset of ejaculation.

WARNINGS

Premature ejaculation may be due to a condition requiring medical supervision. If this product, used as directed, does not provide relief, discontinue use and consult a doctor.
Avoid contact with the eyes or broken skin.
If you or your partner develop a rash or irritation, such as burning or itching, discontinue use. If symptoms persist, consult a doctor.
Do not use during the partner’s pregnancy.

Keep out of reach of children. If product is accidentally swallowed, get medical help or contact a Poison Control Center right away.

DIRECTIONS

- Prior to the coitus apply a thin layer of the cream onto the glans and under it (glans frenulum) and spread by massaging.
- Approximately 5 minutes later the cream will have absorbed well and will have fully developed its effect.
- Prior to the coitus itself, the cream must be unconditionally washed off the penis and glans.
- The effect may be increased by repeated use of the cream shortly before the coitus.

OTHER INFORMATION

- Store in a cool, dry place. Protect from sunlight.

INACTIVE INGREDIENTS

Alanine, Allantoin, Aloe Barbadensis Leaf Juice Powder, Aspartic Acid, Cetearyl Alcohol, Citric Acid, Dextrin, Dimethicone, Ethylhexylglycerin, Fructose, Glucose, Glutamic Acid, Glycerin, Glyceryl Stearate, Hexylene Glycol, Isopropyl Palmitate, Lactic Acid, Laureth-9, Panthenol, Phenoxyethanol, Polyglyceryl-3 Stearate, Potassium Sorbate, Propylene Glycol, Simmondsia Chienesis (Jojoba) Seed Oil, Sodium Benzoate, Sodium Stearoyl Lactylate, Sucrose, Tocopheryl Acetate, Urea, Water, Xanthan Gum